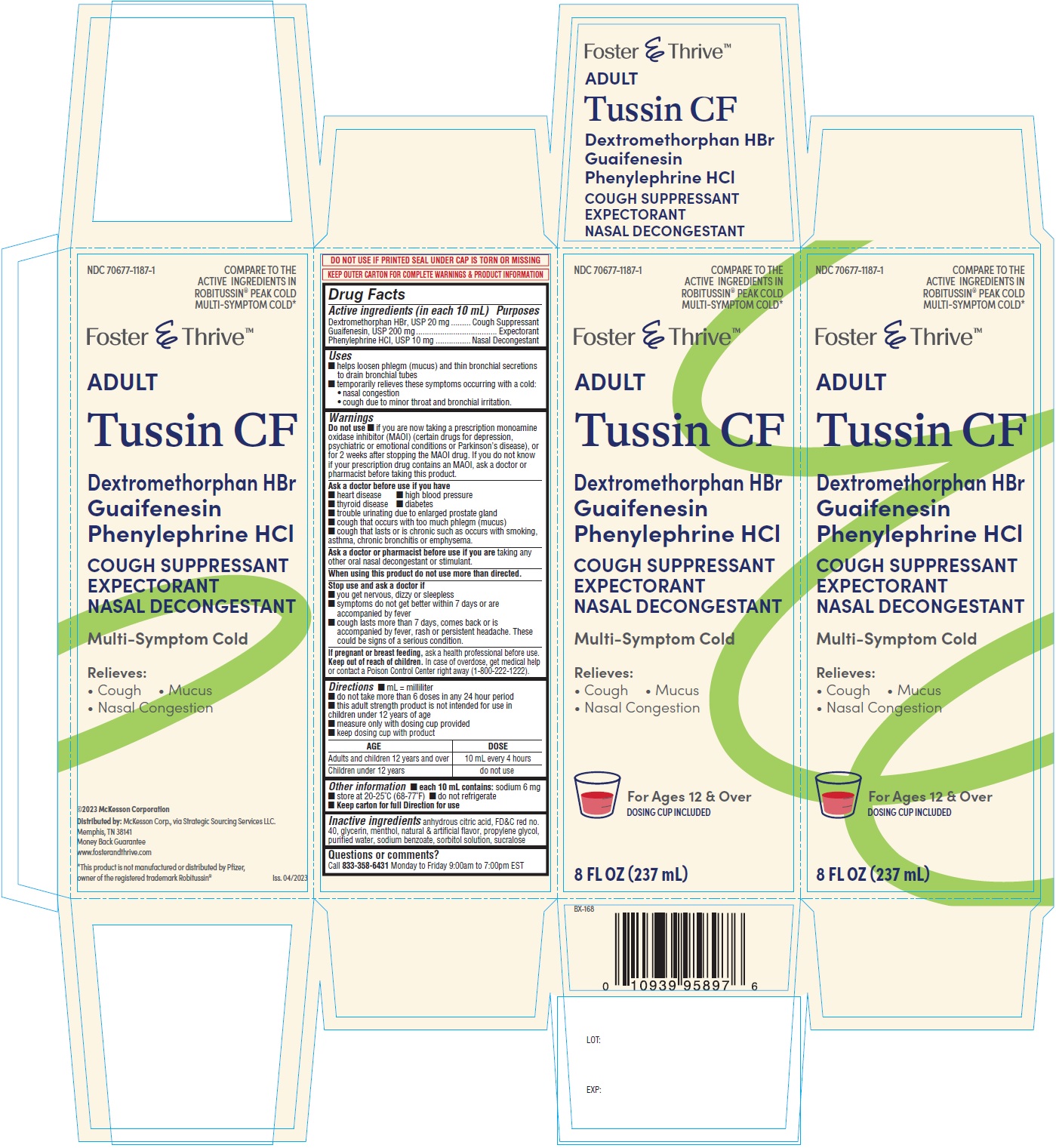 DRUG LABEL: Tussin CF

NDC: 70677-1187 | Form: SOLUTION
Manufacturer: Strategic Sourcing Services
Category: otc | Type: HUMAN OTC DRUG LABEL
Date: 20250107

ACTIVE INGREDIENTS: DEXTROMETHORPHAN HYDROBROMIDE 20 mg/10 mL; GUAIFENESIN 200 mg/10 mL; PHENYLEPHRINE HYDROCHLORIDE 10 mg/10 mL
INACTIVE INGREDIENTS: ANHYDROUS CITRIC ACID; FD&C RED NO. 40; GLYCERIN; MENTHOL; PROPYLENE GLYCOL; WATER; SODIUM BENZOATE; SORBITOL SOLUTION; SUCRALOSE

Tussin CF
Dextromethorphan HBr Guaifenesin Phenylephrine HCl

Active ingredients (in each 10 mL)

Dextromethorphan HBrDextromethorphan HBr, USP 20 mg
Guaifenesin, USP 200 mg
Phenylephrine HCI, USP 10 mg

Purposes

Cough suppressant
Expectorant
Nasal decongestant

Uses

■ helps loosen phlegm (mucus) and thin bronchial secretions to drain bronchial tubes
■ temporarily relieves these symptoms occurring with a cold:
• nasal congestion
• cough due to minor throat and bronchial irritation.

Warnings

Do not use

■ if you are now taking a prescription monoamine oxidase inhibitor (MAOI) (certain drugs for depression, psychiatric or emotional conditions or Parkinson’s disease), or for 2 weeks after stopping the MAOI drug. If you do not know if your prescription drug contains an MAOI, ask a doctor or pharmacist before taking this product.

Ask a doctor before use if you have

■ heart disease ■ high blood pressure
■ thyroid disease ■ diabetes
■ trouble urinating due to enlarged prostate gland
■ cough that occurs with too much phlegm (mucus)
■ cough that lasts or is chronic such as occurs with smoking,asthma, chronic bronchitis or emphysema.

Ask a doctor or pharmacist before use if you are

taking any other oral nasal decongestant or stimulant.

When using this product do not use more than directed.

Stop use and ask a doctor if

■ you get nervous, dizzy or sleepless
■ symptoms do not get better within 7 days or are accompanied by fever
■ cough lasts more than 7 days, comes back or is accompanied by fever, rash or persistent headache. These could be signs of a serious condition.

If pregnant or breast feeding

ask a health professional before use.

Keep out of reach of children

In case of overdose, get medical help or contact a Poison Control Center right away (1-800-222-1222).

Directions

■ mL = milliliter
■ do not take more than 6 doses in any 24 hour period
■ this adult strength product is not intended for use in children under 12 years of age
■ measure only with dosing cup provided
■ keep dosing cup with product

AGE | DOSE
Adults and children 12 years and over | 10 mL every 4 hours
Children under 12 years | do not use

Other information

■ each 10 mL contains: sodium 6 mg
■ store at 20-25°C (68-77°F) ■ do not refrigerate
■ Keep carton for full Direction for use

Inactive ingredients

anhydrous citric acid, FD&C red no.40, glycerin, menthol, natural & artificial flavor, propylene glycol,purified water, sodium benzoate, sorbitol solution, sucralose

Questions or comments?

Call 833-358-6431Monday to Friday 9:00am to 7:00pm EST

©2023 McKesson Corporation
Distributed by:McKesson Corp., via Strategic Sourcing Services LLC.
Memphis, TN 38141
Money Back Guarantee
www.fosterandthrive.com
*This product is not manufactured or distributed by Pfizer,
owner of the registered trademark Robitussin®

PRINCIPAL DISPLAY PANEL

Dextromethorphan HBr Guaifenesin Phenylephrone HCL-237 mL